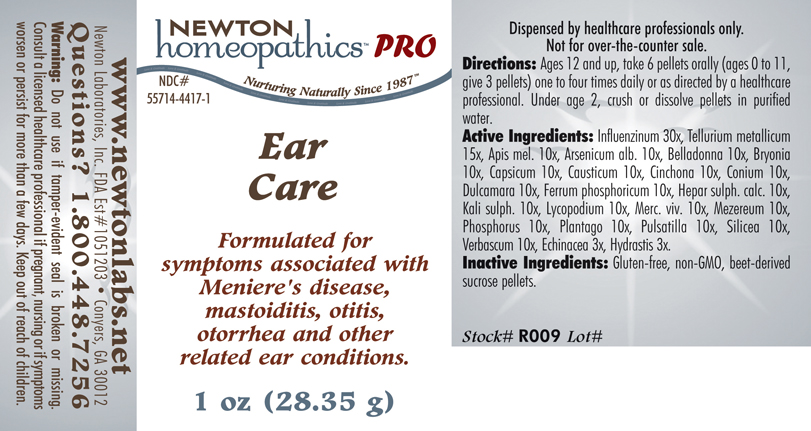 DRUG LABEL: Ear Care 
NDC: 55714-4417 | Form: PELLET
Manufacturer: Newton Laboratories, Inc.
Category: homeopathic | Type: HUMAN PRESCRIPTION DRUG LABEL
Date: 20110601

ACTIVE INGREDIENTS: Influenza A Virus 30 [hp_X]/1 g; Tellurium 15 [hp_X]/1 g; Apis Mellifera 10 [hp_X]/1 g; Arsenic Trioxide 10 [hp_X]/1 g; Atropa Belladonna 10 [hp_X]/1 g; Bryonia Alba Root 10 [hp_X]/1 g; Capsicum 10 [hp_X]/1 g; Causticum 10 [hp_X]/1 g; Cinchona Officinalis Bark 10 [hp_X]/1 g; Conium Maculatum Flowering Top 10 [hp_X]/1 g; Solanum Dulcamara Stem 10 [hp_X]/1 g; Ferrosoferric Phosphate 10 [hp_X]/1 g; Calcium Sulfide 10 [hp_X]/1 g; Potassium Sulfate 10 [hp_X]/1 g; Lycopodium Clavatum Spore 10 [hp_X]/1 g; Mercury 10 [hp_X]/1 g; Daphne Mezereum Bark 10 [hp_X]/1 g; Phosphorus 10 [hp_X]/1 g; Plantago Major 10 [hp_X]/1 g; Pulsatilla Vulgaris 10 [hp_X]/1 g; Silicon Dioxide 10 [hp_X]/1 g; Verbascum Thapsus 10 [hp_X]/1 g; Echinacea, Unspecified 3 [hp_X]/1 g; Goldenseal 3 [hp_X]/1 g; Influenza B Virus 30 [hp_X]/1 g
INACTIVE INGREDIENTS: Sucrose

Ear Care

INDICATIONS & USAGE SECTION

EAR CARE Formulated for symptoms associated with Meniere's disease, mastoiditis, otitis, otorrhea and other related ear conditions.

DOSAGE & ADMINISTRATION SECTION

Directions: Ages 12 and up, take 6 pellets orally (ages 0 to 11, give 3 pellets) one to four times daily or as directed by a healthcare professional. Under age 2, crush or dissolve pellets in purified water.

ACTIVE INGREDIENT SECTION

Influenzinum 30x, Tellurium metallicum 15x, Apis mel. 10x, Arsenicum alb. 10x, Belladonna 10x, Bryonia 10x, Capsicum 10x, Causticum 10x, Cinchona 10x, Conium 10x, Dulcamara 10x, Ferrum phosphoricum 10x, Hepar sulph. calc. 10x, Kali sulph. 10x, Lycopodium 10x, Merc. viv. 10x, Mezereum 10x, Phosphorus 10x, Plantago 10x, Pulsatilla 10x, Silicea 10x, Verbascum 10x, Echinacea 3x, Hydrastis 3x.

INACTIVE INGREDIENT SECTION

Inactive Ingredients: Gluten-free, non-GMO, beet-derived sucrose pellets.

QUESTIONS? SECTION

www.newtonlabs.net Newton Laboratories, Inc. FDA Est # 1051203 - Conyers, GA 30012
Questions? 1.800.448.7256

WARNINGS SECTION

Warning: Do not use if tamper- evident seal is broken or missing. Consult a licensed healthcare professional if pregnant, nursing or if symptoms worsen or persist for more than a few days. Keep out of reach of children.

PREGNANCY OR BREAST FEEDING SECTION

Consult a licensed healthcare professional if pregnant, nursing or if symptoms worsen or persist for more than a few days

KEEP OUT OF REACH OF CHILDREN SECTION

Keep out of reach of children.